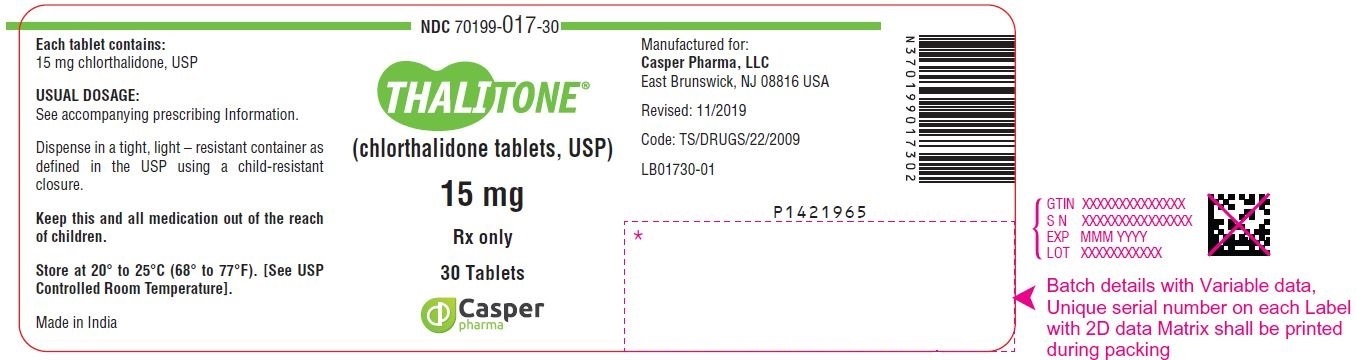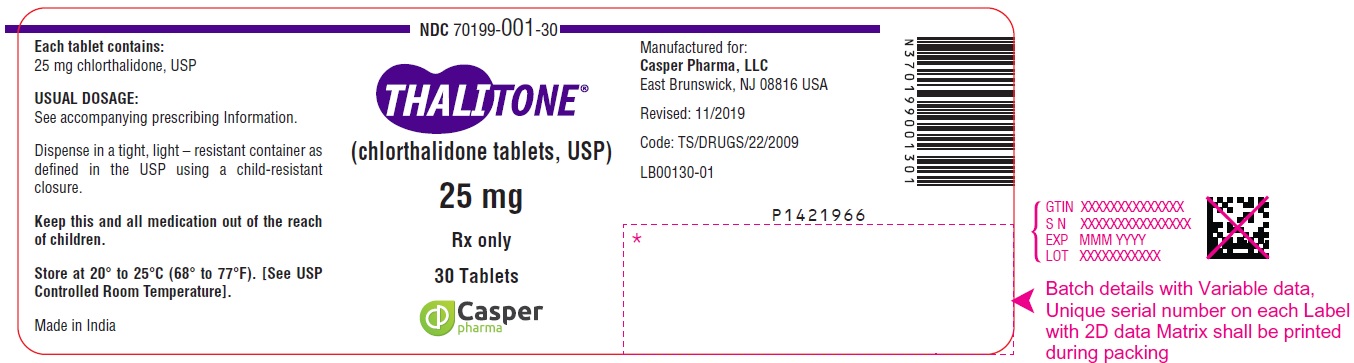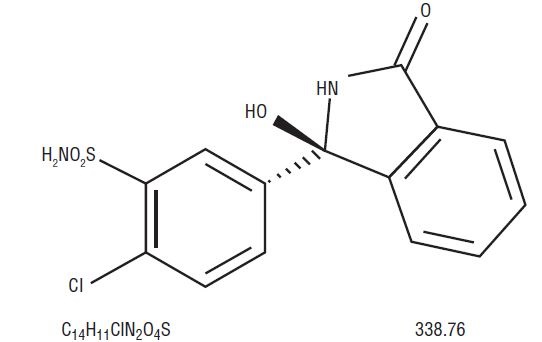 DRUG LABEL: Thalitone
NDC: 70199-017 | Form: TABLET
Manufacturer: Casper Pharma LLC
Category: prescription | Type: Human Prescription Drug Label
Date: 20191230

ACTIVE INGREDIENTS: CHLORTHALIDONE 15 mg/1 1
INACTIVE INGREDIENTS: POVIDONE; LACTOSE MONOHYDRATE; CELLULOSE, MICROCRYSTALLINE; SILICON DIOXIDE; MAGNESIUM STEARATE; SODIUM STARCH GLYCOLATE TYPE A POTATO

HIGHLIGHTS OF PRESCRIBING INFORMATION

These highlights do not include all the information needed to use THALITONE® safely and effectively. See full prescribing information for THALITONE.
THALITONE (chlorthalidone) tablets, for oral use
Initial U.S. Approval: 1988

1 INDICATIONS AND USAGE

THALITONE is a thiazide-like diuretic indicated:
• For the treatment of hypertension, to lower blood pressure. Lowering blood pressure reduces the risk of fatal and nonfatal cardiovascular events, primarily strokes and myocardial infarctions (1.1).
• as adjunctive therapy in edema associated with heart failure, cirrhosis of the liver, and renal disease, including nephrotic syndrome (1.2).

2 DOSAGE AND ADMINISTRATION

• Initiate therapy with the lowest possible dose, then titrate according to individual patient response (2.1).
• Hypertension: Recommended initial dose is 15 mg daily with food. If additional blood pressure reduction is needed, increase the dose to 25 mg (2.2).
• Edema: Recommended initial dose is 50 mg to 100 mg daily or 100 mg on alternate days. Depending on response, dosage can be decreased or increased up to a maximum of 200 mg daily (2.3).

3 DOSAGE FORMS AND STRENGTHS

Tablets: 15 mg and 25 mg (3).

4 CONTRAINDICATIONS

• Anuria (4).
• Hypersensitivity (4).

5 WARNINGS AND PRECAUTIONS

• Hypotension: Higher risk for patients with impaired sympathetic response, volume-depletion or salt restriction (5.1).
• Renal Impairment: Patients with pre-existing kidney disease may be at higher risk. (5.2).
• Monitor serum electrolytes periodically (5.3).

6 ADVERSE REACTIONS

The most frequently expected adverse drug reactions among patients receiving THALITONE are hypotension, dizziness, renal dysfunction, and electrolyte abnormalities (6).
To report SUSPECTED ADVERSE REACTIONS, contact Casper Pharma LLC at 1-844-5-CASPER (1-844-522-7737) or FDA at 1-800-FDA-1088 or www.fda.gov/medwatch.

7 DRUG INTERACTIONS

• Antihypertensive drugs: Chlorthalidone may add to or potentiate the action of other antihypertensive drugs (7).
• Lithium: Lithium renal clearance is reduced by chlorthalidone, increasing the risk of lithium toxicity (7).

8 USE IN SPECIFIC POPULATIONS

• Pregnancy: May cause fetal harm (8.1).
• Lactation: Breastfeeding not recommended (8.2).
• Pediatrics: Safety and efficacy in children have not been established (8.4).
• Geriatric Use: No overall difference in responses versus younger patients but care should be taken in dose selection in patients with impaired renal function (8.5).

FULL PRESCRIBING INFORMATION

1 INDICATIONS AND USAGE

1.1 Hypertension

THALITONE® is indicated for the treatment of hypertension, to lower blood pressure. Lowering blood pressure reduces the risk of fatal and nonfatal cardiovascular events, primarily strokes and myocardial infarctions. These benefits have been seen in controlled trials of antihypertensive drugs from a wide variety of pharmacologic classes including the class to which this drug principally belongs. There are no controlled trials demonstrating risk reduction with THALITONE.
Control of high blood pressure should be part of comprehensive cardiovascular risk management, including, as appropriate, lipid control, diabetes management, antithrombotic therapy, smoking cessation, exercise, and limited sodium intake. Many patients will require more than one drug to achieve blood pressure goals. For specific advice on goals and management, see published guidelines, such as those of the National High Blood Pressure Education Program’s Joint National Committee on Prevention, Detection, Evaluation, and Treatment of High Blood Pressure (JNC).
Numerous antihypertensive drugs, from a variety of pharmacologic classes and with different mechanisms of action, have been shown in randomized controlled trials to reduce cardiovascular morbidity and mortality, and it can be concluded that it is blood pressure reduction, and not some other pharmacologic property of the drugs, that is largely responsible for those benefits. The largest and most consistent cardiovascular outcome benefit has been a reduction in the risk of stroke, but reductions in myocardial infarction and cardiovascular mortality also have been seen regularly.
Elevated systolic or diastolic pressure causes increased cardiovascular risk, and the absolute risk increase per mmHg is greater at higher blood pressures, so that even modest reductions of severe hypertension can provide substantial benefit. Relative risk reduction from blood pressure reduction is similar across populations with varying absolute risk, so the absolute benefit is greater in patients who are at higher risk independent of their hypertension (for example, patients with diabetes or hyperlipidemia), and such patients would be expected to benefit from more aggressive treatment to a lower blood pressure goal.
THALITONE can be used alone or in combination with other antihypertensive agents.

1.2 Edema

Chlorthalidone is indicated in adults as adjunctive therapy in edema associated with heart failure, cirrhosis of the liver, and renal disease, including nephrotic syndrome.

2 DOSAGE AND ADMINISTRATION

2.1 General Considerations

THALITONE cannot be substituted with other formulations of chlorthalidone.
Initiate therapy with the lowest possible dose, then titrate according to individual patient response.

2.2 Hypertension

The initial recommended dose is 15 mg once daily with food. After 2 weeks, the dosage may be increased to a single daily dose of 25 mg if additional blood pressure reduction is needed. Doses above 25 mg are not expected to result in increased blood pressure reduction.

2.3 Edema

The recommended initial dosage is 50 to 100 mg daily or 100 mg on alternate days. Depending on response, dosage can be decreased or increased up to a maximum of 200 mg daily.

3 DOSAGE FORMS AND STRENGTHS

THALITONE 15 mg tablets are white biconvex, kidney shaped tablets with “L” on lower punch and “96” on the upper punch.
THALITONE 25 mg tablets are white biconvex, kidney shaped tablets with “L” on one side and “99” on the other side.

4 CONTRAINDICATIONS

THALITONE is contraindicated in patients with anuria or hypersensitivity to chlorthalidone or other sulfonamide-derived drugs.

5 WARNINGS AND PRECAUTIONS

5.1 Hypotension

THALITONE may cause symptomatic hypotension. Patients with impaired sympathetic response, volume-depletion or who are salt restricted may be at increased risk for developing hypotension.
If hypotension occurs, place the patient in the supine position and, if necessary, give intravenous normal saline. A transient hypotensive response is not a contraindication to further treatment, which usually can be continued without difficulty once the blood pressure has stabilized.

5.2 Impaired Renal Function

Changes in renal function including acute renal failure can be caused by diuretics. Patients with chronic kidney disease, heart failure, or volume depletion may be at particular risk of developing acute renal failure on THALITONE. Monitor renal function periodically. Consider withholding or discontinuing therapy in patients who develop a clinically significant decrease in renal function on THALITONE [see Drug Interactions (7)].

5.3 Electrolyte Abnormalities

THALITONE can cause hypokalemia, hyponatremia, hypochloremic alkalosis, and hypomagnesemia. Hypomagnesemia can result in hypokalemia which appears difficult to treat despite potassium repletion. Monitor serum electrolytes periodically.
If hypokalemia is accompanied by clinical signs (e.g., muscular weakness, paresis, or ECG alterations), THALITONE should be discontinued. Correction of hypokalemia and any coexisting hypomagnesemia is recommended prior to the initiation of thiazides.

5.4 Metabolic Disturbances

Chlorthalidone may alter glucose tolerance.
Chlorthalidone may raise serum levels of cholesterol and triglycerides.
Chlorthalidone may raise the serum uric acid level due to reduced clearance of uric acid and may cause or exacerbate hyperuricemia and precipitate gout in susceptible patients.
Chlorthalidone decreases urinary calcium excretion and may cause elevations of serum calcium. Monitor calcium levels in patients with hypercalcemia receiving THALITONE.

6 ADVERSE REACTIONS

The following adverse reactions are described in more detail elsewhere in the label;
• Hypotension [see Warnings and Precautions (5.1)]
• Impaired Renal Function [see Warnings and Precautions (5.2)]
• Electrolyte Abnormalities [see Warnings and Precautions (5.3)]
• Metabolic Disturbances [see Warnings and Precautions (5.4)]
The following adverse reactions have been observed, but there is not enough systematic collection of data to support an estimate of their frequency.
Gastrointestinal System Reactions: anorexia, gastric irritation, nausea, vomiting, cramping, diarrhea, constipation, jaundice (intrahepatic cholestatic jaundice), pancreatitis.
Central Nervous System Reactions: dizziness, paresthesias, headache.
Hematologic Reactions: leukopenia, agranulocytosis, thrombocytopenia, aplastic anemia.
Dermatologic-Hypersensitivity Reactions: purpura, photosensitivity, rash, urticaria, necrotizing angiitis (vasculitis) (cutaneous vasculitis), Lyell’s syndrome (toxic epidermal necrolysis).
Cardiovascular Reaction: Orthostatic hypotension.
Other Adverse Reactions: muscle spasm, weakness, restlessness, impotence, xanthopsia.

7 DRUG INTERACTIONS

Effect of chlorthalidone on other drugs
Chlorthalidone may add to or potentiate the action of other antihypertensive drugs.
Chlorthalidone and related drugs may increase the responsiveness to tubocurarine.
Lithium renal clearance is reduced by chlorthalidone, increasing the risk of lithium toxicity. Monitor serum lithium levels during concomitant use.

8 USE IN SPECIFIC POPULATIONS

8.1 Pregnancy

Risk Summary
Available data over decades from observational studies and reports with chlorthalidone use in pregnant women have not identified a drug-associated risk of major birth defects or miscarriage. However, adverse fetal outcomes, including fetal or neonatal jaundice, thrombocytopenia, hypoglycemia, and electrolyte abnormalities have been reported following maternal use of thiazide diuretics (see Clinical Considerations). Chlorthalidone should not be used as first-line therapy to treat hypertension in pregnancy. Advise pregnant women of the potential risk to a fetus.
The estimated background risk of major birth defects and miscarriage for the indicated population is unknown. All pregnancies have a background risk of birth defect, loss, or other adverse outcomes. In the U.S. general population, the estimated background risks of major birth defects and miscarriage in clinically recognized pregnancies is 2 to 4% and 15 to 20%, respectively.
Clinical Considerations
Disease-associated maternal and/or embryo/fetal risk
Hypertension in pregnancy increases the maternal risk for pre-eclampsia, gestational diabetes, premature delivery, and delivery complications (e.g., need for cesarean section, and post-partum hemorrhage). Hypertension increases the fetal risk for intrauterine growth restriction and stillbirth.
Fetal/Neonatal Adverse Reactions
Thiazides can cross the placenta, and concentrations reached in the umbilical vein approach those in the maternal plasma. Thiazides, like other diuretics, can cause placental hypoperfusion. Use of thiazides during pregnancy is associated with a risk of fetal or neonatal jaundice, thrombocytopenia, hypoglycemia, and electrolyte abnormalities. Thiazides do not prevent or alter the course of EPH (Edema, Proteinuria, Hypertension) gestosis (pre-eclampsia) and should not be used as first-line therapy to treat hypertension in pregnant women.
Data
Animal Data
Reproduction studies have been performed in the rat and the rabbit and have revealed no evidence of harm to the fetus due to chlorthalidone.The available data do not allow the calculation of comparisons between the exposure of chlorthalidone observed in animal studies to the systemic exposure that would be expected in humans.

8.2 Lactation

Risk Summary
Chlorthalidone is present in human milk. There is no information regarding the effects of chlorthalidone on the breastfed infant or the effects on milk production. Because of the potential for chlorthalidone accumulation which may lead to serious adverse reactions in the breastfed infant (such as jaundice, thrombocytopenia, hyperglycemia, electrolyte abnormalities), advise patients that breastfeeding is not recommended during treatment with chlorthalidone.

8.4 Pediatric Use

Safety and effectiveness in children have not been established.

8.5 Geriatric Use

Clinical studies of THALITONE did not include sufficient numbers of subjects aged 65 and over to determine whether they respond differently from younger subjects. Other reported clinical experience has not identified differences in responses between the elderly and younger patients. In general, dose selection for an elderly patient should be cautious, usually starting at the low end of the dosing range, reflecting the greater frequency of decreased hepatic, renal or cardiac function, and of concomitant disease or other drug therapy.
This drug is known to be substantially excreted by the kidney, and the risk of toxic reactions to this drug may be greater in patients with impaired renal function. Because elderly patients are more likely to have decreased renal function, care should be taken in dose selection, and it may be useful to monitor renal function.

10 OVERDOSAGE

Symptoms of acute overdosage include nausea, weakness, dizziness and disturbances of electrolyte balance. The oral LD50 of the drug in the mouse and the rat is more than 25,000 mg/kg body weight. The minimum lethal dose (MLD) in humans has not been established. There is no specific antidote but gastric lavage is recommended, followed by supportive treatment. Where necessary, this may include intravenous dextrose-saline with potassium, administered with caution.

11 DESCRIPTION

THALITONE (chlorthalidone USP) is an antihypertensive/diuretic supplied as 15 mg and 25 mg tablets for oral use. It is a monosulfamyl diuretic that differs chemically from thiazide diuretics in that a double ring system is incorporated in its structure. It is a racemic mixture of 2-chloro-5-(1-hydroxy-3-oxo-1-isoindolinyl) benzenesulfonamide, with the following structural formula:

Chlorthalidone is practically insoluble in water, in ether and in chloroform; soluble in methanol; slightly soluble in alcohol.
The inactive ingredients are colloidal silicon dioxide, lactose monohydrate, magnesium stearate, microcrystalline cellulose, povidone, sodium starch glycolate.

12 CLINICAL PHARMACOLOGY

12.1 Mechanism of Action

Chlorthalidone is a long-acting oral diuretic with antihypertensive activity. The diuretic effects of chlorthalidone and the benzothiadiazine (thiazide) diuretics appear to arise from similar mechanisms and the maximal effect of chlorthalidone and the thiazides appear to be similar. The site of the action appears to be the distal convoluted tubule of the nephron. Although the mechanism of action of chlorthalidone and related drugs is not wholly clear, sodium and water depletion appear to provide a basis for its antihypertensive effect.

12.2 Pharmacodynamics

The diuretic action of chlorthalidone commences a mean of 2.6 hours after dosing and continues for up to 72 hours. The drug produces diuresis with increased excretion of sodium and chloride. The diuretic effects of chlorthalidone lead to decreased extracellular fluid volume, plasma volume, cardiac output, total exchangeable sodium, glomerular filtration rate, and renal plasma flow. Chlorthalidone produces dose-related reductions in serum potassium levels, elevations in serum uric acid and blood glucose, and it can lead to decreased sodium and chloride levels.

12.3 Pharmacokinetics

Absorption
THALITONE (chlorthalidone USP) has been formulated with PVP (povidone polyvinylpyrrolidone), a bioavailability enhancer that provides 104% to 116% bioavailability relative to an oral solution of chlorthalidone [see Clinical Studies (14)]. THALITONE cannot be substituted with other formulations of chlorthalidone.
Distribution
In the blood, approximately 75% of the drug is bound to plasma proteins over a concentration range of 0.2 to 7.7 ug/mL.
Elimination
The mean plasma half-life of chlorthalidone is about 40 to 60 hours. It is eliminated primarily as unchanged drug in the urine.

13 NONCLINICAL TOXICOLOGY

13.1 Carcinogenesis & Mutagenesis & Impairment Of Fertility

No information is available.

14 CLINICAL STUDIES

Two similarly designed, 12-week, double-blind, parallel group, placebo-controlled multicenter studies were conducted to compare THALITONE 15 mg to the standard chlorthalidone 25 mg in terms of reduction in blood pressure and metabolic disturbances. Collectively, a total of 222 patients with long-standing diastolic blood pressure between 90 and 104 mm Hg were randomized to receive THALITONE 15 mg (N=71), standard chlorthalidone 25 mg (N=75), or placebo (N=76).
THALITONE 15 mg has the advantage of demonstrating potentially fewer metabolic disturbances (Table 1) in particular, lowered glucose levels when compared to Hygroton® 25 mg in clinical setting (Table 2). THALITONE 15 mg helps meet the goal of lowering blood pressure in patients that respond to Chlorthalidone therapy. In general, electrolyte abnormalities are a class effect associated with Chlorthalidone therapy.
Table 1. Reduction in blood pressure at 12 weeks (THALITONE 15 mg vs. Standard chlorthalidone 25 mg)

Pairwise comparison | 2 through 12 weeks |  | 4 through 12 weeks
Pairwise comparison | Mean change (95% CI) | Significance level | Mean change (95% CI) | Significance level
Standing SBP, mm Hg
THALITONE 15 mg vs. placebo | −11.77 vs. −1.89 (−13.02, −6.74) | <0.001 | −12.43 vs. −2.02 (−13.87, −6.95) | <0.001
THALITONE 15 mg vs. standard chlorthalidone 25 mg | −11.77 vs. −11.73 (−3.18, 3.1) | 0.98 | −12.43 vs. −11.70 (−4.19, 2.73) | 0.68
Standing DBP, mm Hg
THALITONE 15 mg vs. placebo | −5.95 vs. −3.28 (−4.5, −0.84) | <0.01 | −6.64 vs. −3.42 (−5.29, −1.15) | <0.01
THALITONE 15 mg vs. standard chlorthalidone 25 mg | − 5.95 vs. −6.79 (−0.99, 2.67) | 0.37 | −6.64 vs. −7.06 (−1.65, 2.49) | 0.69
Supine SBP, mm Hg
THALITONE 15 mg vs. placebo | −8.42 vs. −2.63 (−8.87, −2.71) | <0.001 | −8.91 vs. −2.85 (-9.46, -2.66) | <0.001
THALITONE 15 mg vs. standard chlorthalidone 25 mg | −8.42 vs. −10.31 (−1.19, 4.97) | 0.23 | −8.91 vs. −10.61 (−1.70, 5.10) | 0.33
Supine DBP, mm Hg
THALITONE 15 mg vs. placebo | −6.44 vs. −4.16 (−4.46, −0.11) | 0.04 | −6.72 vs. −4.28 (−4.85, −0.03) | 0.05
THALITONE 15 mg vs. standard chlorthalidone 25 mg | −6.44 vs. −6.82 (−1.80, 2.56) | 0.73 | −6.72 vs. −7.05 (−2.08, 2.74) | 0.79

SBP: systolic blood pressure, DBP: diastolic blood pressure, CI: confidence interval
Table 2. Mean changes in laboratory parameters (THALITONE 15 mg vs. Standard chlorthalidone 25 mg)

Parameter | THALITONE 15 mg |  | Standard chlorthalidone 25 mg | Placebo
Potassium (mmol/L)
Baseline | N/A |  | N/A | N/A
4 Weeks | −0.35 (0.08)* |  | −0.53 (0.05)* | 0.10 (0.05)
12 Weeks | −0.31 (0.07)* |  | −0.55 (0.06)* | 0.12 (0.06)
Cholesterol (mg/dL)
Baseline | N/A |  | N/A | N/A
4 Weeks | 5.51 (3.70)* |  | 5.14 (3.29)* | −7.18 (3.30)
12 Weeks | 9.34 (3.03) |  | 8.11 (3.86) | 0.26 (4.53)
Glucose (mg/dL)
Baseline | N/A |  | N/A | N/A
4 Weeks | 1.83 (2.55) |  | 6.56 (2.36) | 1.52 (2.17)
12 Weeks | −0.84 (2.58)^+ |  | 11.02 (2.71)* | −1.83 (2.29)
Uric Acid (mg/dL)
Baseline | N/A | N/A |  | N/A
4 Weeks | 0.66 (0.16)* | 1.04 (0.14)* |  | −0.34 (0.15)
12 Weeks | 0.71 (0.13)* | 1.10 (0.14)* |  | −0.19 (0.15)

*p<0.05 vs. placebo
+p<0.05 vs. standard chlorthalidone 25 mg
N/A: Not Applicable

16 HOW SUPPLIED/STORAGE AND HANDLING

THALITONE (chlorthalidone) Tablets USP 15 mg are white biconvex, kidney shaped tablets with “L” on lower punch and “96” on the upper punch.
Bottles of 30 NDC 70199-017-30
Bottles of 100 NDC 70199-017-01
THALITONE (chlorthalidone) Tablets USP 25 mg are white biconvex, kidney shaped tablets with “L” on one side and “99” on the other side.
Bottles of 30 NDC 70199-001-30
Bottles of 100 NDC 70199-001-01
Store at 20o to 25oC (68o to 77oF). [See USP Controlled Room Temperature].
Dispense in a tight, light-resistant container as defined in the USP using a child-resistant closure.

17 PATIENT COUNSELING INFORMATION

• Patients should inform their doctor if they have had an allergic reaction to chlorthalidone or other diuretics; kidney disease; gout; been taking lithium carbonate.
• Patients should be cautioned to contact their physician if they experience any of the following symptoms of potassium loss: excess thirst, tiredness, drowsiness, restlessness, muscle pains or cramps, nausea, vomiting or increased heart rate or pulse.
• Patients should inform their doctor if they have symptoms of light-headedness or dizziness.
• Pregnancy
Advise a pregnant woman of the potential risk to a fetus. Advise females of reproductive potential to inform their prescriber of a known or suspected pregnancy [see Use in Specific Populations (8.1)].
• Lactation
Advise females not to breastfeed during treatment with chlorthalidone [see Use in Specific Populations (8.2)].
Rx Only
PIB00101-05
Manufactured for:
Casper Pharma LLC
East Brunswick, NJ 08816
Made in India.
Revised: 12/2019

PACKAGE LABEL.PRINCIPAL DISPLAY PANEL

Thalitone® (chlorthalidone tablets USP) 15 mg
Bottles of 30 NDC 70199-017-30

Thalitone® (chlorthalidone tablets USP) 25 mg
Bottles of 30 NDC 70199-001-30